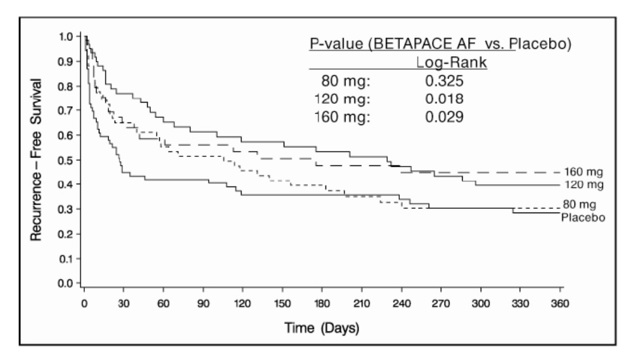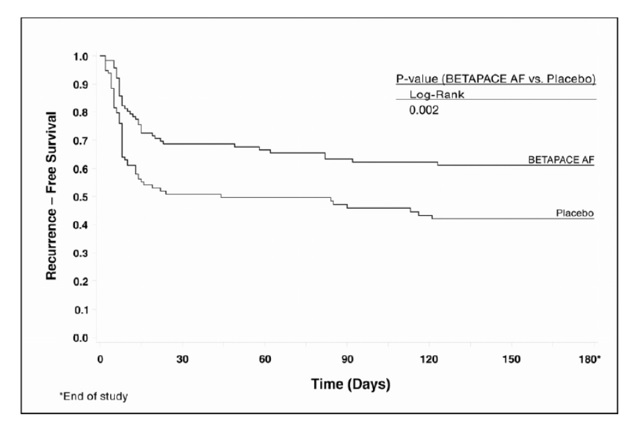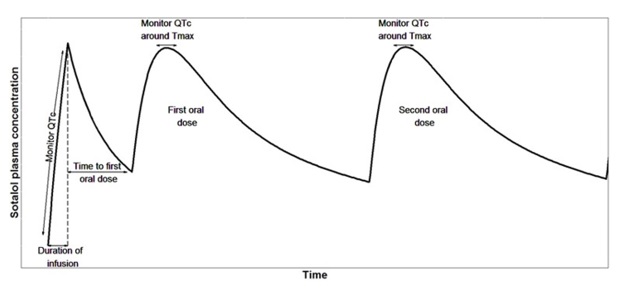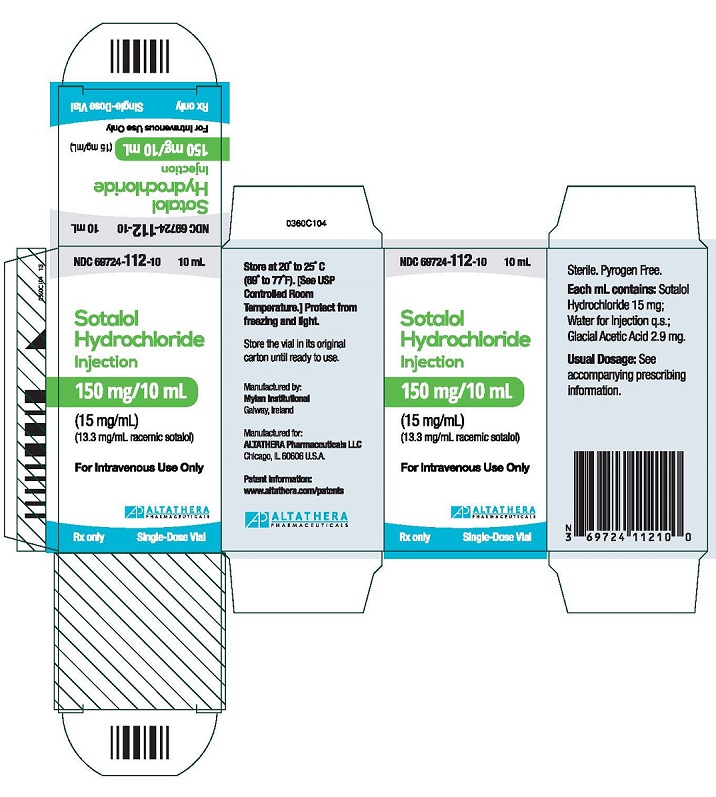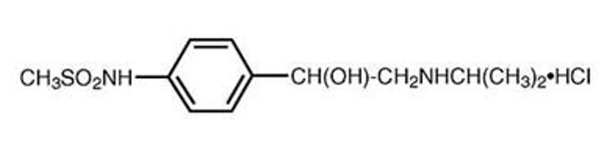 DRUG LABEL: Sotalol hydrochloride
NDC: 69724-112 | Form: INJECTION
Manufacturer: ALTATHERA Pharmaceuticals, LLC
Category: prescription | Type: HUMAN PRESCRIPTION DRUG LABEL
Date: 20250731

ACTIVE INGREDIENTS: SOTALOL HYDROCHLORIDE 15 mg/1 mL
INACTIVE INGREDIENTS: ACETIC ACID 2.9 mg/1 mL; WATER; SODIUM HYDROXIDE

HIGHLIGHTS OF PRESCRIBING INFORMATION

These highlights do not include all the information needed to use SOTALOL HYDROCHLORIDE injection safely and effectively. See full prescribing information for SOTALOL HYDROCHLORIDE.
SOTALOL HYDROCHLORIDE injection, for intravenous use
Initial U.S. Approval: 1992

WARNING: LIFE THREATENING PROARRHYTHMIA

See full prescribing information for complete boxed warning.

- Sotalol can cause life threatening ventricular tachycardia associated with QT interval prolongation. (5.1)
- Initiate or reinitiate in a facility that can provide cardiac resuscitation and continuous electrocardiographic monitoring. (2.3)
- Do not initiate intravenous sotalol therapy if the baseline QTc is longer than 450 ms. If the QTc prolongs to 500 ms or greater, reduce the dose or discontinue. (2.3)

RECENT MAJOR CHANGES

Dosage and Administration (2.2) 7/2025

1 INDICATIONS AND USAGE

Sotalol is an antiarrhythmic indicated for:

- the treatment of life-threatening ventricular tachycardia. (1.1)
- the maintenance of normal sinus rhythm in patients with atrial fibrillation or flutter (AFIB/AFL). (1.2)

Limitations of Use

- Sotalol has not been shown to enhance survival in patients with life-threatening ventricular arrhythmias. (1.1)
- Avoid use in patients with minimally symptomatic or easily reversible AFIB/AFL (1.2)

2 DOSAGE AND ADMINISTRATION

- Intravenous sotalol can substitute for oral sotalol using a regimen that mimics oral exposure (2.2)
- Under close medical monitoring, intravenous sotalol can be used to achieve near steady-state exposure to sotalol prior to initiating or increasing oral dosing. (2.3)
- Recommended dosage depends on target oral dose and creatinine clearance. Refer to full prescribing information. (2.2, 2.3, 2.4)

3 DOSAGE FORMS AND STRENGTHS

Injection: 10-mL vial containing sotalol hydrochloride 150 mg (3)

4 CONTRAINDICATIONS

- Bradyarrhythmia, sick sinus syndrome or 2nd or 3rd degree atrioventricular (AV) block without a pacemaker (4)
- Congenital or acquired long QT syndrome (4)
- Cardiogenic shock or decompensated heart failure (4)
- Serum potassium < 4mEq (4)
- Bronchial asthma or related bronchospastic conditions (4)
- Hypersensitivity to sotalol (4)

5 WARNINGS AND PRECAUTIONS

- QT prolongation, risk of life-threatening ventricular arrhythmias, particularly torsade de pointes (5.1)
- Bradyarrhythmia, AV block, sick sinus syndrome (5.2, 5.3)
- Negative inotropy: hypotension, heart failure (5.4, 5.5)
- Bronchospasm (5.6)
- Masked hypoglycemia (5.7)
- Masked hyperthyroidism (5.8)
- Anaphylaxis (5.9)

6 ADVERSE REACTIONS

Bradycardia, dyspnea, fatigue, QTc prolongation

To report SUSPECTED ADVERSE REACTIONS, contact AltaThera Pharmaceuticals LLC at 1-800-524-1985 or FDA at 1-800-FDA-1088 or www.fda.gov/medwatch.

7 DRUG INTERACTIONS

- Additive to other negative chronotropes (7.2, 7.3, 7.4)
- Additive to other QT-prolonging drugs (7.1, 7.2)
- Antagonizes effect of beta-agonists (7.6)

FULL PRESCRIBING INFORMATION

WARNING: LIFE THREATENING PROARRHYTHMIA

Sotalol can cause life threatening ventricular tachycardia associated with QT interval prolongation. To minimize the risk of drug induced arrhythmia, initiate or up-titrate intravenous sotalol in a facility that can provide continuous electrocardiographic monitoring and cardiac resuscitation [see Dosage and Administration (2.3) and Warnings and Precautions (5.1)]

Do not initiate intravenous sotalol therapy if the baseline QTc is longer than 450 ms. If the QTc prolongs to 500 ms or greater, reduce the dose or discontinue.

1 INDICATIONS AND USAGE

1.1 Life-Threatening Ventricular Arrhythmia

Sotalol is indicated for the treatment of documented, life-threatening ventricular arrhythmias, such as sustained ventricular tachycardia in adult and pediatric patients.

Limitations of Use:

Sotalol has not been shown to enhance survival in patients with life-threatening ventricular arrhythmias.

1.2 Delay in Recurrence of Atrial Fibrillation/Atrial Flutter

Sotalol is indicated for the maintenance of normal sinus rhythm (delay in time to recurrence of atrial fibrillation/atrial flutter (AFIB/AFL)) in adults and pediatric patients with highly symptomatic AFIB/AFL who are currently in sinus rhythm.

Limitation of Use:

Because sotalol can cause life-threatening ventricular arrhythmias, reserve its use for patients in whom AFIB/AFL is highly symptomatic.

2 DOSAGE AND ADMINISTRATION

2.1 General Considerations and Safety Measures

For either indication, intravenous sotalol can substitute for oral sotalol in patients unable to take oral drugs or be used to achieve steady state concentration faster compared to the conventional oral dosing.

Intravenous sotalol must be diluted for infusion. Parenteral drug products should be inspected visually for particulate matter and discoloration prior to administration, whenever solution and container permit. Dilute intravenous sotalol in Sodium Chloride Injection, 5% Dextrose Injection, or Lactated Ringer’s Injection. Choose a volume convenient for administration and consistent with fluid restriction. Use a volumetric infusion pump.

Patients should be initiated or re-initiated on intravenous sotalol in a facility that can provide cardiac resuscitation and continuous electrocardiographic monitoring.

Withdraw other antiarrhythmic drug therapy before starting intravenous sotalol if the patient's clinical condition permits. Perform a baseline ECG to determine the QTc interval and measure and normalize serum potassium and magnesium levels before initiating therapy. If the baseline QTc is >450 ms, sotalol is contraindicated. Assess renal function in order to establish the appropriate dosing interval. Monitor QTc 2 to 4 hours after each up-titration in dose [see Dosage and Administration (2.3) and Use in Specific Populations (8.6)].

2.2 Use for Substitution of Oral Sotalol

To match the exposure to oral sotalol, intravenously infuse the adjusted dose at the same dosing frequency as the oral dose based on glomerular filtration rate (see Table 1) over 5 hours.

Table 1: Intravenous doses for sotalol infusion when used as a substitute for oral sotalol [Individual GFR should be derived as follows: 〖GFR〗_i= eGFR/1.73 ×BSA; whereby, eGFR is GFR estimated by a GFR estimating equation, and BSA is individual body surface area.]
Current Oral dose | Dose of intravenous sotalol based on GFR
 | GFR 60 mL/min | GFR 30 to < 60 mL/min | GFR 10 to < 30 mL/min
80 mg | 75 mg every 12 hours | 67.5 mg every 24 hours | 67.5 mg every 36 to 48 hours
120 mg | 112.5 mg every 12 hours | 105 mg every 24 hours | 105 mg every 36 to 48 hours
160 mg | 150 mg every 12 hours | 142.5 mg every 24 hours | 135 mg every 36 to 48 hours

2.3 Use for Loading Dose

Initiate or up-titrate intravenous sotalol in a facility that can provide continuous ECG monitoring and cardiac resuscitation. Personnel should be trained in the management of serious ventricular arrhythmias. Withdraw other antiarrhythmic therapy before starting sotalol hydrochloride.

Measure and normalize serum potassium and magnesium levels before initiation. If the baseline QTc is >450 ms (JT >330 ms if QRS over 100 ms), sotalol is contraindicated.

The intravenous loading dose depends on the target oral dose and estimated glomerular filtration rate; the dosing interval for oral administration of sotalol and the minimum delay between the end of the infusion and the first oral dose also depend on renal function; see Table 2 [see Clinical Studies (14.4)].

Infuse the loading dose over one hour. Monitor QTc interval every 15 minutes during infusion. Continue to monitor QTc at peak serum concentration (2 to 4 hours post-dose) following the first oral dose (in all patients) and second oral dose (in patients with GFR ≥60 mL/min). If the QTc interval prolongs to >500 ms or increases 20% from baseline when initiating for an oral dose of 80 mg twice daily, discontinue drug; if initiating for an oral dose of 120 mg twice daily discontinue drug and consider a lower dose. If re-initiation at a lower dose of 80 mg is desired, wait at least 1 day (in patients with GFR >60 mL/min), or at least 3 days (in patients with GFR ≤60 to >30 mL/min), or 7 days (in patients with GFR ≤30 to >10 mL/min).

Table 2: Recommended Loading Dosage in Adults
GFR [Individual GFR should be derived as follows: 〖GFR〗_i= eGFR/1.73 ×BSA; whereby, eGFR is GFR estimated by eGFR estimating equations, and BSA is individual body surface area.] [mL/min] | Intravenous loading dose [mg] to be administered over 1 hour when the oral dose is going from |  |  |  | Minimum delay to first oral dose [hours] | Oral dosing interval [hours]
GFR [Individual GFR should be derived as follows: 〖GFR〗_i= eGFR/1.73 ×BSA; whereby, eGFR is GFR estimated by eGFR estimating equations, and BSA is individual body surface area.] [mL/min] | Sotalol Initiation |  | Sotalol Escalation |  | Minimum delay to first oral dose [hours] | Oral dosing interval [hours]
GFR [Individual GFR should be derived as follows: 〖GFR〗_i= eGFR/1.73 ×BSA; whereby, eGFR is GFR estimated by eGFR estimating equations, and BSA is individual body surface area.] [mL/min] | 0 to 80 mg [Recommended starting dose] | 0 to 120 mg | 80 mg to 120 mg | 120 mg to 160 mg | Minimum delay to first oral dose [hours] | Oral dosing interval [hours]
≥90 | 60 | 90 | 75 | 90 | 4 | 12
60- to <90 | 82.5 | 125 | 82.5 | 105 | 4 | 12
30- to <60 | 75 | 112.5 | 82.5 | 105 | 6 | 24
10- to <30 | 75 | 112.5 | 82.5 | 105 | 12 | 48

2.4 Use in Pediatric Patients

Table 3 shows suggested starting doses in pediatric patients with normal renal function.

Table 3. Suggesting starting doses [mg/kg] in children with normal renal function.
Age | Dose [mg/kg]
3 days | 0.32
6 days | 0.51
9 days | 0.69
12 days | 0.81
2 weeks | 0.9
3 weeks | 1
1 month to 6 years | 1.2
6-12 years | 1.1
>12 years | 0.95

3 DOSAGE FORMS AND STRENGTHS

Injection: 150 mg/10 mL (15 mg/mL) single-dose vial containing sotalol hydrochloride (3)

4 CONTRAINDICATIONS

Sotalol hydrochloride is contraindicated in patients with:

- Sinus bradycardia (<50 bpm), sick sinus syndrome or second or third degree atrioventricular (AV) block without a pacemaker [See Warnings and Precautions (5.2, 5.3)]
- Congenital or acquired long QT syndromes, QTc interval >450 ms [See Warnings and Precautions (5.1)]
- Cardiogenic shock, decompensated heart failure [See Warnings and Precautions (5.5)]
- Serum potassium <4 mEq/L [See Warnings and Precautions (5.1)]
- Bronchial asthma or related bronchospastic conditions [See Warnings and Precautions (5.6)]
- Known hypersensitivity to sotalol [See Warnings and Precautions (5.9)]

5 WARNINGS AND PRECAUTIONS

5.1 Proarrhythmia

Sotalol can cause serious and potentially fatal ventricular arrhythmias , primarily Torsade de Pointes (TdP), a polymorphic ventricular tachycardia associated with QTc prolongation. QTc prolongation is directly related to the concentration of sotalol. Factors such as reduced renal function, female sex, higher dose, bradycardia, history of sustained ventricular tachycardia (VT) or ventricular fibrillation (VF), atrial fibrillation with sinus node dysfunction, and heart failure increase the risk of TdP. The risk of TdP can be reduced by adjustment of the sotalol dose according to renal function and by monitoring the ECG for excessive increases in QTc.

Correct hypokalemia or hypomagnesemia prior to initiating sotalol hydrochloride, as these conditions can increase the degree of QTc prolongation and potential for TdP. Special attention should be given to electrolyte and acid-base balance in patients experiencing severe or prolonged diarrhea or patients receiving concomitant diuretic drugs.

Proarrhythmic events should be anticipated upon initiating therapy and with every up-titration of sotalol.

Avoid sotalol with other drugs known to cause QTc prolongation [see Dosage and Administration (2.1) and Drug Interactions (7.1)].

5.2 Bradycardia/Atrioventricular (AV) Block

Sotalol can cause bradycardia, sinus pauses or sinus arrest. Sotalol-induced bradycardia increases the risk of Torsade de Pointes, particularly following cardioversion. Monitor the ECG in patients receiving concomitant negative chronotropes [see Drug Interactions (7.2, 7.3, 7.4)] .

5.3 Sick Sinus Syndrome

Sotalol is contraindicated in patients with sick sinus syndrome, because it may cause sinus bradycardia, sinus pauses, or sinus arrest. Sotalol augments bradycardia and QTc prolongation following cardioversion.

5.4 Hypotension

Sotalol produces significant reductions in both systolic and diastolic blood pressures. Monitor hemodynamics during administration.

5.5 Heart Failure

New onset or worsening heart failure may occur during initiation or up-titration of sotalol because of its beta-blocking effects. Monitor for signs and symptoms of heart failure and discontinue treatment if symptoms occur.

5.6 Bronchospasm

Avoid beta-blockers, like sotalol, in patients with bronchospastic diseases. If sotalol is required, use the smallest effective dose.

5.7 Hypoglycemia

Beta-blockade may prevent early warning signs of hypoglycemia, such as tachycardia, and increase the risk for severe or prolonged hypoglycemia at any time during treatment, especially in patients with diabetes mellitus or pediatric patients who are fasting (i.e., surgery, not eating regularly, or vomiting). Monitor blood glucose as appropriate.

5.8 Thyroid Abnormalities

Avoid abrupt withdrawal of beta-blockade which might be followed by an exacerbation of symptoms of hyperthyroidism, including thyroid storm. Beta-blockade may mask certain clinical signs (e.g., tachycardia) of hyperthyroidism.

5.9 Anaphylaxis

While taking beta-blockers, patients with a history of anaphylactic reaction to a variety of allergens may have a more severe reaction on repeated challenge, either accidental, diagnostic, or therapeutic. Such patients may be unresponsive to the usual doses of epinephrine used to treat the allergic reaction.

5.10 Anesthesia

The impaired ability of the heart to respond to reflex adrenergic stimuli may augment the risks of general anesthesia and surgical procedures.

6 ADVERSE REACTIONS

The following adverse reactions are described elsewhere:

- Proarrhythmia [see Warnings and Precautions (5.1, 5.2)]
- Negative inotropy [see Warnings and Precautions (5.3, 5.4)]

Adverse reactions related to sotalol use are those which are typical of its Class II (beta- blocking) and Class III (cardiac action potential duration prolongation) effects. The common documented beta-blocking adverse reactions (bradycardia, dyspnea, and fatigue) and Class III effects (QT interval prolongation) are dose related.

7 DRUG INTERACTIONS

7.1 Antiarrhythmic and other QT Prolonging Drugs

Withdraw other Class I or Class III antiarrhythmic agents prior to dosing with sotalol. Class Ia antiarrhythmic drugs, such as disopyramide, quinidine, and procainamide, and other Class III drugs (for example, amiodarone) are not recommended as concomitant therapy, because of their potential for additive QTc prolongation [see Warnings and Precautions (5.1)].

7.2 Negative Chronotropes

Both digitalis glycoside and beta-blockers slow atrioventricular conduction and decrease heart rate. Concomitant use can increase the risk of bradycardia.

7.3 Calcium Blocking Drugs

Sotalol and calcium blocking drugs can be expected to have additive effects slowing atrioventricular conduction, ventricular function, and blood pressure.

7.4 Catecholamine-Depleting Agents

Concomitant use of catecholamine-depleting drugs, such as reserpine and guanethidine, with a beta- blocker may produce an excessive reduction of resting sympathetic nervous tone. Monitor such patients for hypotension and marked bradycardia which may produce syncope.

7.5 Insulin and Oral Antidiabetics

Hyperglycemia may occur, and the dosage of insulin or antidiabetic drugs may require adjustment. Symptoms of hypoglycemia may be masked.

7.6 Beta-2-Receptor Stimulants

Beta-agonists such as albuterol, terbutaline and isoproterenol may have to be administered in increased dosages when used concomitantly with sotalol.

7.7 Clonidine

Concomitant use with sotalol increases the risk of bradycardia. Because beta-blockers may potentiate the rebound hypertension sometime observed after clonidine discontinuation, withdraw sotalol several days before the gradual withdrawal of clonidine to reduce the risk of rebound hypertension.

7.8 Drug/Laboratory Test Interactions

The presence of sotalol in the urine may result in falsely elevated levels of urinary metanephrine when measured by fluorimetric or photometric methods.

8 USE IN SPECIFIC POPULATIONS

8.1 Pregnancy

Risk Summary

Both the untreated underlying condition in pregnancy and the use of sotalol in pregnancy cause adverse outcomes to the mother and fetus/neonate (see Clinical Considerations). In animal reproduction studies in rats, early resorptions were increased at 15 times the maximum recommended human dose (MRHD). In rabbits an increase in fetal death was observed at 2 times the MRHD administered as single dose. Sotalol did not reveal any teratogenic potential in rats or rabbits at 15 and 2 times the MRHD respectively (see Data).

All pregnancies have a background risk of birth defect, loss, or other adverse outcomes. The estimated background risk of major birth defects and miscarriage for the indicated population is unknown. In the United States (U.S.) general population, the estimated background risk of major birth defects and miscarriage in clinically recognized pregnancies is 2% to 4% and 15% to 20%, respectively.

Clinical Considerations

The incidence of VT is increased and may be more symptomatic during pregnancy. Most tachycardia episodes are initiated by ectopic beats and the occurrence of arrhythmia episodes may, therefore, increase during pregnancy. Breakthrough arrhythmias may also occur during pregnancy, as therapeutic treatment levels may be difficult to maintain due to the increased volume of distribution and increased drug metabolism inherent in the pregnant state.

Fetal/Neonatal Adverse Reactions

Sotalol has been shown to cross the placenta and is found in amniotic fluid. From published observational studies, the potential fetal adverse effects of sotalol use during pregnancy are growth restriction, transient fetal bradycardia, hyperbilirubinemia, hypoglycemia, uterine contractions, and possible intrauterine death. Sotalol may have a greater effect on QT prolongation in the immature heart than in the adult heart, and therefore, conveys an increased risk of serious fetal arrhythmia and/or possible intrauterine death. Monitor the newborn for symptoms of beta blockade.

Labor or Delivery

Generally, risk of arrhythmias increases during the labor and delivery process; therefore, considering the proarrhythmia potential of the drug, patients treated with sotalol should be monitored continuously during labor and delivery.

Data

Animal Data

Reproduction studies in rats and rabbits administered sotalol during organogenesis at 15 times and 2 times the MRHD as mg/m ^2, respectively, did not reveal any teratogenic potential associated with sotalol.

In pregnant rats, sotalol doses administered during organogenesis at approximately15 times the MRHD as mg/m ^2, increased the number of early resorptions, while no increase in early resorptions was noted at 2 times the MRHD as mg/m ^2.

In reproductive studies in rabbits, a sotalol dose (160 mg/kg/day) at 5 times the MRHD as mg/m ^2 produced a slight increase in fetal death, and maternal toxicity. However, one study from published data reported an increase in fetal deaths in rabbits receiving a single dose (50 mg/kg) at 2 times the MRHD as mg/m ^2 as on gestation day 14.

8.2 Lactation

Risk Summary

Limited available data from published literature report that sotalol is present in human milk. The estimated daily infant dose of sotalol received from breastmilk is 0.8-3.4 mg/kg, estimated at 22 to 25.5% of the maternal weight-adjusted dosage of sotalol (see Data). The amount of the drug in breast milk is similar to the neonatal therapeutic dosage. Therefore, there is potential for bradycardia and other symptoms of beta blockade such as dry mouth, skin or eyes, diarrhea or constipation in the breastfed infant. There is no information regarding the effects of sotalol on milk production. Because of the potential serious adverse reactions to the breastfed child and the high level of sotalol in breast milk, advise women not to breastfeed while on treatment with sotalol.

Data

Sotalol is present in human milk in high levels. A prospective study evaluated 20 paired samples of breast milk and maternal blood from 5 mothers who elected to breastfeed. Breast milk samples had a mean sotalol concentration of 10.5 µg/mL (± 1.1 µg/mL; range: 4.8 to 20.2 µg/mL) compared to a simultaneous mean maternal plasma concentration of 2.3 µg/mL (± 0.3 µg/mL; range: 0.8 to 5.0 µg/mL). The mean milk plasma ratio was 5.4:1 (range: 2.2 to 8.8). The estimated daily infant dose was 0.8-3.4 mg/kg, estimated at 22 to 25.5% of the maternal weight-adjusted dosage of sotalol. This is similar to recommended therapeutic dose in neonates. None of the mothers reported any adverse reactions in the breastfed infant.

8.3 Females and Males of Reproductive Potential

Infertility

Based on the published literature, beta blockers (including sotalol) may cause erectile dysfunction.

8.4 Pediatric Use

Sotalol is indicated for:

- The treatment of documented, life-threatening VT in pediatric patients.
- The maintenance of normal sinus rhythm [delay in time to recurrence of atrial fibrillation/atrial flutter (AFIB/AFL)] in pediatric patients with highly symptomatic AFIB/AFL who are currently in sinus rhythm.

The Class III electrophysiologic and beta-blocking effects, the pharmacokinetics, and the relationship between the effects (QTc interval and resting heart rate) and drug concentrations have been evaluated in pediatric patients between 3 days and 12 years of age [see Clinical Pharmacology (12.3)].

Side effects from use of other sotalol-containing drug products in pediatric patients are those typical of a beta blocking agent, and led to discontinuation of the drug in 3 to 6% of patients. As in adults, the Class III antiarrhythmic action of sotalol in pediatric patients is associated with a significant proarrhythmic potential. In pediatric patients, the incidence of proarrhythmic side effects of sotalol varies from 0 to 22%; and the smallest pediatric patients tended to exhibit greater QTc-prolongation [see Clinical Pharmacology (12.2)] ].

Proarrhythmic effects of sotalol in pediatric patients included increased ventricular ectopy and exacerbation of bradycardia, the latter predominantly in patients with sinus node dysfunction following surgery for congenital cardiac defects. Bradycardia may require emergency pacemaker implantation. Close inpatient monitoring is recommended until steady state drug levels are achieved [see Dosage and Administration (2.1, 2.3)].

8.6 Renal Impairment

Sotalol is eliminated predominantly via the kidney [see Clinical Pharmacology (12.3)]. Sotalol exposure increases with decrease in renal function. Sotalol dose should be reduced and interval between doses should be increased based on the patient’s renal function [see Dosage and Administration (2.2, 2.3)].

10 OVERDOSAGE

Overdosage with sotalol may be fatal.

Symptoms and Treatment of Overdosage: The most common signs to be expected are bradycardia, congestive heart failure, hypotension, bronchospasm and hypoglycemia. In cases of massive intentional overdosage (2-16 grams) of sotalol the following clinical findings were seen: hypotension, bradycardia, cardiac asystole, prolongation of the QTc interval, Torsade de Pointes, ventricular tachycardia, and premature ventricular complexes. If overdosage occurs, therapy with sotalol should be discontinued and the patient observed closely. Because of the lack of protein binding, hemodialysis is useful for reducing sotalol plasma concentrations. Patients should be carefully observed until QTc intervals are normalized and the heart rate returns to levels >50 bpm. The occurrence of hypotension following an overdose may be associated with an initial slow drug elimination phase (half-life of 30 hours) thought to be due to a temporary reduction of renal function caused by the hypotension. In addition, if required, the following therapeutic measures are suggested:

Bradycardia or Cardiac Asystole: | Atropine, another anticholinergic drug, a beta-adrenergic agonist (e.g., isoproterenol) or transvenous cardiac pacing.
AV Block: | (second and third degree) transvenous cardiac pacemaker.
Hypotension: | (depending on associated factors) epinephrine rather than isoproterenol or norepinephrine may be useful.
Bronchospasm: | Aminophylline or aerosol beta-2-receptor stimulant. Higher than normal doses of beta-2 stimulus may be required.
Torsade de Pointes: | DC cardioversion, magnesium sulfate, potassium replacement. Once Torsade de Pointes is terminated, transvenous cardiac pacing or an isoproterenol infusion to increase heart rate can be employed.

11 DESCRIPTION

Sotalol hydrochloride injection is an aqueous formulation of sotalol hydrochloride for intravenous use. Sotalol is an antiarrhythmic drug with Class II (beta-adrenoreceptor blocking) and Class III (cardiac action potential duration prolongation) properties.

Sotalol hydrochloride is a white, crystalline solid with a molecular weight of 308.8. It is hydrophilic, soluble in water, propylene glycol and ethanol, but is only slightly soluble in chloroform. Chemically, sotalol hydrochloride is d, l- N - [4-[1-hydroxy-2-[(1-methylethyl) amino] ethyl] phenyl] methane-sulfonamide monohydrochloride. The molecular formula is C 12 H 20 N 2 O 3S•HCl and is represented by the following structural formula:

Intravenous sotalol Injection is supplied as a sterile, clear solution in a 10 mL single-dose vial, for intravenous administration after dilution. Each vial contains 150 mg racemic sotalol hydrochloride (equivalent to 132.8 mg racemic sotalol) in sodium acetate buffer. The sotalol hydrochloride concentration of the formulation is 15 mg/mL. Each mL contains 2.9 mg glacial acetic acid in water for injection as an inactive ingredient. The pH of the injection is adjusted with sodium hydroxide to be between 6.0 and 7.0.

12 CLINICAL PHARMACOLOGY

12.1 Mechanism of Action

Sotalol has both beta-adrenoreceptor blocking (Vaughan Williams Class II) and cardiac action potential duration prolongation (Vaughan Williams Class III) antiarrhythmic properties. Intravenous sotalol is a racemic mixture of d- and l-sotalol. Both isomers have similar Class III antiarrhythmic effects, while the l-isomer is responsible for virtually all of the beta-blocking activity.

The beta-blocking effect of sotalol is non-cardioselective, half maximal at oral doses of about 80 mg/day and maximal at oral doses between 320 and 640 mg/day. Significant beta-blockade occurs at oral doses as low as 25 mg, significant Class III effects can be seen after a single oral or IV dose of 80 or 75 mg respectively.

In pediatric patients, a Class III electrophysiologic effect can be seen at daily doses of 210 mg/m^2 body surface area (BSA). A reduction of the resting heart rate due to the beta-blocking effect of sotalol is observed at daily doses ≥90 mg/m^2 in pediatric patients.

12.2 Pharmacodynamics

Electrophysiology: Sotalol prolongs the plateau phase of the cardiac action potential in the isolated myocyte, as well as in isolated tissue preparations of ventricular or atrial muscle (Class III activity). In intact animals it slows heart rate, decreases AV nodal conduction and increases the refractory periods of atrial and ventricular muscle and conduction tissue.

In man, the Class II (beta-blockade) electrophysiological effects of sotalol include increased sinus cycle length (slowed heart rate), decreased AV nodal conduction, and increased AV nodal refractoriness. The Class III electrophysiological effects in man include prolongation of the atrial and ventricular monophasic action potentials, and effective refractory period prolongation of atrial muscle, ventricular muscle, and atrio-ventricular accessory pathways (when present) in both the anterograde and retrograde directions. With oral doses of 160 to 640 mg/day, the surface ECG shows dose-related mean increases of 40-100 ms in QT and 10-40 ms in QTc.

Twenty-five pediatric patients in an unblinded, multicenter trial with supraventricular (SVT) and/or ventricular (VT) tachyarrhythmias, aged between 3 days and 12 years (mostly neonates and infants), received an ascending titration regimen with daily oral doses of 30, 90 and 210 mg/m^2 with dosing every 8 hours for a total of 9 doses. During steady-state, the respective average increases above baseline of the QTc interval were 2, 14, and 29 ms at the 3 dose levels. The respective mean maximum increases in QTc above baseline were 23, 36, and 55 ms. The steady-state percent increases in the RR interval were 3, 9 and 12%. The smallest pediatric patients (BSA <0.33 m^2) showed a tendency for larger Class III effects (ΔQTc) and an increased frequency of prolongations of the QTc interval compared with pediatric patients with BSA ≥0.33 m^2. The beta-blocking effects also tended to be greater in the smaller pediatric patients (BSA<0.33 m^2).

Hemodynamics: In a study of systemic hemodynamic function measured invasively in 12 patients with a mean LV ejection fraction of 37% and ventricular tachycardia (9 sustained and 3 non-sustained), a median dose of 160 mg twice daily of sotalol produced a 28% reduction in heart rate and a 24% decrease in cardiac index at 2 hours post-dosing at steady-state. Concurrently, systemic vascular resistance and stroke volume showed non-significant increases of 25% and 8%, respectively.

Pulmonary capillary wedge pressure increased significantly from 6 to 12 mmHg in the 11 patients who completed the study. Mean arterial pressure, mean pulmonary artery pressure and stroke work index did not significantly change. Exercise and isoproterenol induced tachycardia are antagonized by sotalol, and total peripheral resistance increases by a small amount.

In hypertensive patients, sotalol produces significant reductions in both systolic and diastolic blood pressures. Although sotalol is usually well-tolerated hemodynamically, in patients with marginal cardiac compensation, deterioration in cardiac performance may occur [see Warnings and Precautions (5.5)].

12.3 Pharmacokinetics

The pharmacokinetics of the d and l isomers of sotalol are essentially identical.

Absorption

In healthy subjects, the oral bioavailability of sotalol is >90%. After oral administration, peak plasma concentrations are reached in 2.5 to 4 hours, and steady-state plasma concentrations are attained within 2-3 days (i.e., after 5-6 doses when administered twice daily). Over the oral dosage range 160-640 mg/day, sotalol displays dose proportionality with respect to plasma concentrations. When administered with a standard meal, the absorption of sotalol was reduced by approximately 20% compared to administration in the fasting state.

Distribution

With oral dosing, distribution occurs to a central (plasma) and to a peripheral compartment, with a mean elimination half-life of 12 hours. Dosing every 12 hours results in trough plasma concentrations which are approximately one-half of those at peak.

Sotalol does not bind to plasma proteins and is not metabolized. Sotalol shows very little intersubject variability in plasma levels. Sotalol crosses the blood brain barrier poorly.

Elimination

Metabolism

Sotalol is not metabolized and is not expected to inhibit or induce any CYP 450 enzymes.

Excretion

Excretion is predominantly via the kidney through glomerular filtration and to a small degree by tubular secretion in the unchanged form.

Specific Populations

Geriatric

Age per se does not significantly alter the pharmacokinetics of sotalol, but impaired renal function in geriatric patients can increase the terminal elimination half-life, resulting in increased drug accumulation.

Pediatric

The combined analysis of two unblinded, multicenter trials (a single dose and a multiple dose study) using an oral solid dosage form of sotalol in 59 pediatric patients, aged between 3 days and 12 years, showed the pharmacokinetics of sotalol to be first order. A daily dose of 30 mg/ m ^2 of sotalol was administered in the single dose study and daily doses of 30, 90 and 210 mg/ m ^2 were administered every 8 hours in the multi-dose study. After rapid absorption with peak levels occurring on average between 2-3 hours following administration, sotalol was eliminated with a mean half-life of 9.5 hours. Steady-state was reached after 1-2 days. The average peak to trough concentration ratio was 2. BSA was the most important covariate and more relevant than age for the pharmacokinetics of sotalol. The smallest pediatric patients (BSA <0.33 m^2) exhibited a greater drug exposure (+59%) than the larger pediatric patients who showed a uniform drug concentration profile. The intersubject variation for oral clearance was 22%.

Patients with Renal Impairment

There is a direct relationship between renal function, as measured by creatinine clearance (CrCL based on the Cockcroft-gault equation) or glomerular filtration rate (GFR based on the MDRD and CKD-EPI equations), and the elimination rate of sotalol. The half-life of sotalol is prolonged (up to 69 hours) in anuric patients. Following oral sotalol administration every 12 hours, steady state Cmax was increased by 45% in patients with CrCL 60-90 mL/min compared to patients with CrCL >90 mL/min. Compared to oral sotalol administered every 12 hours in patients with CrCL > 90 mL/min, steady state Cmax was increased by 30% when oral sotalol was administered every 24 hours in patients with CrCL 30-60 mL/min and every 48 hours in patients with CrCL 10-30 mL/min. The corresponding IV doses in patients with impaired renal function were identified based on matching exposure for each oral dose level. The sotalol clearance vs CrCL relationship was incorporated in a population pharmacokinetic model of sotalol and used for selection of doses of injectable sotalol that match exposures provided by approved doses of oral sotalol. Analyses were conducted to assess whether using different renal function estimation methods (i.e., CrCL based on the Cockcroft-Gault equation versus GFR based on the MDRD and CKD-EPI equations) resulted in the same relationship between renal function and the elimination of sotalol. The results indicate that either method leads to the same dosing recommendations (i.e., the level of renal function at which a dose adjustment should be made is the same, regardless of the method used).

Patients with Hepatic Impairment

Since sotalol is not subject to first-pass metabolism, patients with hepatic impairment show no alteration in clearance of sotalol.

Drug Interaction Studies

Antacids

Administration of oral sotalol within 2 hours of antacids may result in a reduction in Cmax and AUC of 26% and 20%, respectively, and consequently in a 25% reduction in the bradycardic effect at rest.

Administration of the antacid two hours after oral sotalol has no effect on the pharmacokinetics or pharmacodynamics of sotalol.

No pharmacokinetic interactions were observed with hydrochlorothiazide or warfarin.

13 NONCLINICAL TOXICOLOGY

13.1 Carcinogenesis, Mutagenesis, Impairment of Fertility

No evidence of carcinogenic potential was observed in rats during a 24-month study at 137-275 mg/kg/ day (approximately 30 times the maximum recommended human oral dose (MRHD) as mg/kg or 5 times the MRHD as mg/ m^2) or in mice, during a 24-month study at 4141-7122 mg/kg/day (approximately 450- 750 times the MRHD as mg/kg or 36-63 times the MRHD as mg/ m^2).

Sotalol has not been evaluated in any specific assay of mutagenicity or clastogenicity.

No significant reduction in fertility occurred in rats at oral doses of 1000 mg/kg/day (approximately 100 times the MRHD as mg/kg or 9 times the MRHD as mg/ m^2) prior to mating, except for a small reduction in the number of offspring per litter. Reproduction studies in rats and rabbits during organogenesis at 100 and 22 times the MRHD as mg/kg (9 and 7 times the MRHD as mg/ m^2), respectively, did not reveal any teratogenic potential associated with sotalol HCl. In rabbits, a high dose of sotalol HCl (160 mg/kg/day) at 16 times the MRHD as mg/kg (6 times the MRHD as mg/ m^2) produced a slight increase in fetal death likely due to maternal toxicity. Eight times the maximum dose (80 mg/kg/day or 3 times the MRHD as mg/ m^2) did not result in an increased incidence of fetal deaths. In rats, 1000 mg/kg/day sotalol HCl, 100 times the MRHD (18 times the MRHD as mg/ m^2), increased the number of early resorptions, while at 14 times the maximum dose (2.5 times the MRHD as mg/ m^2), no increase in early resorptions was noted. However, animal reproduction studies are not always predictive of human response.

14 CLINICAL STUDIES

14.1 Clinical Studies in Ventricular Arrhythmias with Oral Sotalol

Sotalol has been studied in life-threatening and less severe arrhythmias. In patients with frequent premature ventricular complexes (VPC), orally administered sotalol was significantly superior to placebo in reducing VPCs, paired VPCs and non-sustained ventricular tachycardia (NSVT); the response was dose-related through 640 mg/day with 80-85% of patients having at least a 75% reduction of VPCs. Sotalol was also superior, at the doses evaluated, to propranolol (40-80 mg TID) and similar to quinidine (200-400 mg QID) in reducing VPCs. In patients with life-threatening arrhythmias [sustained VT/VF], sotalol was studied acutely [by suppression of programmed electrical stimulation (PES) induced VT and by suppression of Holter monitor evidence of sustained VT] and, in acute responders, chronically.

In a double-blind, randomized comparison of oral sotalol and procainamide given intravenously (total of 2 mg/kg sotalol vs. 19 mg/kg of procainamide over 90 minutes), sotalol suppressed PES induction of VT/VF in 30% of patients vs. 20% for procainamide (p=0.2).

In a randomized clinical trial [Electrophysiologic Study Versus Electrocardiographic Monitoring (ESVEM) Trial] comparing choice of antiarrhythmic therapy by PES suppression vs. Holter monitor selection (in each case followed by treadmill exercise testing) in patients with a history of sustained VT/VF who were also inducible by PES, the effectiveness acutely and chronically of sotalol was compared with 6 other drugs (procainamide, quinidine, mexiletine, propafenone, and imipramine). Overall response, limited to first randomized drug, was 39% for sotalol and 30% for the pooled other drugs. Acute response rate for first drug randomized using suppression of PES induction was 36% for sotalol vs. a mean of 13% for the other drugs. Using the Holter monitoring endpoint (complete suppression of sustained VT, 90% suppression of NSVT, 80% suppression of VPC pairs, and at least 70% suppression of VPCs), sotalol yielded 41% response vs. 45% for the other drugs combined. Among responders placed on long term therapy identified acutely as effective (by either PES or Holter), sotalol, when compared to the pool of other drugs, had the lowest two-year mortality (13% vs. 22%), the lowest two-year VT recurrence rate (30% vs. 60%), and the lowest withdrawal rate (38% vs. about 75-80%). The most commonly used doses of sotalol in this trial were 320-480 mg/day (66% of patients), with 16% receiving 240 mg/day or less and 18% receiving 640 mg or more.

It cannot be determined, however, in the absence of a controlled comparison of sotalol vs. no pharmacologic treatment (e.g., in patients with implanted defibrillators) whether sotalol response causes improved survival or identifies a population with a good prognosis.

Sotalol has not been shown to enhance survival in patients with ventricular arrhythmias.

14.2 Clinical Studies in Supra-Ventricular Arrhythmias with Oral Sotalol

Orally administered sotalol has been studied in patients with symptomatic AFIB/AFL in two principal studies, one in patients with primarily paroxysmal AFIB/AFL, the other in patients with primarily chronic AFIB.

In one study, a U.S. multicenter, randomized, placebo-controlled, double-blind, dose-response trial of patients with symptomatic primarily paroxysmal AFIB/AFL, three fixed dose levels of sotalol (80, 120, and 160 mg) twice daily and placebo were compared in 253 patients. In patients with reduced creatinine clearance (40-60 mL/min) the same doses were given once daily. Patients were not randomized for the following reasons: QTc >450 ms; creatinine clearance <40 mL/min; intolerance to beta-blockers; bradycardia-tachycardia syndrome in the absence of an implanted pacemaker; AFIB/AFL was asymptomatic or was associated with syncope, embolic CVA or TIA; acute myocardial infarction within the previous 2 months; congestive heart failure; bronchial asthma or other contraindications to beta-blocker therapy; receiving potassium losing diuretics without potassium replacement or without concurrent use of ACE-inhibitors; uncorrected hypokalemia (serum potassium <3.5 mEq/L) or hypomagnesemia (serum magnesium <1.5 mEq/L); received chronic oral amiodarone therapy for >1 month within previous 12 weeks; congenital or acquired long QTc syndromes; history of Torsade de Pointes with other antiarrhythmic agents which increase the duration of ventricular repolarization; sinus rate <50 bpm during waking hours; unstable angina pectoris; receiving treatment with other drugs that prolong the QT interval; and AFIB/AFL associated with the Wolff-Parkinson-White (WPW) syndrome. If the QTc interval increased to ≥520 ms the drug was discontinued. The patient population in this trial was 64% male, and the mean age was 62 years. No structural heart disease was present in 43% of the patients. Doses were administered once daily in 20% of the patients because of reduced creatinine clearance.

Sotalol was shown to prolong the time to the first symptomatic, ECG-documented recurrence of AFIB/AFL, as well as to reduce the risk of such recurrence at both 6 and 12 months. The 120 mg dose was more effective than 80 mg, but 160 mg did not appear to have an added benefit. Note that these doses were given twice or once daily, depending on renal function. The results are shown in Figure 1 and Tables 4 and 5.

Figure 1. Study 1—Time to First ECG-Documented Recurrence of Symptomatic AFIB/AFL Since Randomization

Table 4: Study 1 - Patient Status at 12 Months
 | Placebo | Oral Sotalol Dose
 |  | 80 mg | 120 mg | 160 mg
Randomized | 69 | 59 | 63 | 62
On treatment in NSR at 12 months without recurrence * | 23% | 22% | 29% | 23%
Recurrence *,† | 67% | 58% | 49% | 42%
D/C for AEs | 6% | 12% | 18% | 29%

AE = adverse event; D/C = discontinuation; NSR = normal sinus rhythm

* Symptomatic AFIB/AFL
† Efficacy endpoint of Study 1; study treatment stopped.

Note that columns do not add up to 100% due to discontinuations for other reasons.

Table 5: Study 1 - Median Time to Recurrence of Symptomatic AFIB/AFL and Relative Risk (vs. Placebo) at 12 Months
 | Placebo | Oral Sotalol Dose
 |  | 80 mg | 120 mg | 160 mg
P-value vs. placebo |  | p=0.325 | p=0.018 | p=0.029
Relative Risk (RR) to placebo |  | 0.81 | 0.59 | 0.59
Median Time to Recurrence (days) | 27 | 106 | 229 | 175

Discontinuation because of adverse events was dose related.

In a second multicenter, randomized, placebo-controlled, double-blind study of 6 months duration in 232 patients with chronic AFIB, sotalol was titrated over a dose range from 80 mg/day to 320 mg/day. The patient population of this trial was 70% male with a mean age of 65 years. Structural heart disease was present in 49% of the patients. All patients had chronic AFIB for >2 weeks but <1 year at entry with a mean duration of 4.1 months. Patients were excluded if they had significant electrolyte imbalance, QTc >460 ms, QRS >140 ms, any degree of AV block or functioning pacemaker, uncompensated cardiac failure, asthma, significant renal disease (estimated creatinine clearance <50 mL/min), heart rate <50 bpm, myocardial infarction or open heart surgery in past 2 months, unstable angina, infective endocarditis, active pericarditis or myocarditis, ≥3 DC cardioversions in the past, medications that prolonged QT interval, and previous amiodarone treatment. After successful cardioversion patients were randomized to receive placebo (n=114) or sotalol (n=118), at a starting dose of 80 mg twice daily. If the initial dose was not tolerated it was decreased to 80 mg once daily, but if it was tolerated it was increased to 160 mg twice daily. During the maintenance period 67% of treated patients received a dose of 160 mg twice daily, and the remainder received doses of 80 mg once daily (17%) and 80 mg twice daily (16%).

Figure 2 and Tables 6 and 7 show the results of the trial. There was a longer time to ECG-documented recurrence of AFIB and a reduced risk of recurrence at 6 months compared to placebo.

Table 6: Study 2 - Patient Status at 6 Months
Randomized | Oral Sotalol | Placebo
 | 118 | 114
On treatment in NSR at 6 months without recurrence * | 45% | 29%
Recurrence *,† | 49% | 67%
Discontinue for AEs | 6% | 3%
Death |  | 1%

* Symptomatic or asymptomatic AFIB/AFL
† Efficacy endpoint of Study 2; study treatment stopped.

Table 7: Study 2 - Median Time to Recurrence of Symptomatic AFIB/AFL/Death and Relative Risk (vs. Placebo) at 6 Months
p-value vs. placebo | Oral Sotalol | Placebo
 | p=0.002
Relative Risk (RR) to placebo Median time to recurrence (days) | 0.55
 | >180 | 44

Figure 2. Study 2—Time to First ECG-Documented Recurrence of Symptomatic AFIB/AFL/Death Since Randomization

14.3 Intravenous Loading Dosage

Computer-based simulations incorporating sotalol dose-exposure-QTc relationships were used to derive the intravenous loading doses. Based on these simulations, the intravenous loading dose in a typical patient across each of the renal function categories is expected to achieve steady state concentration faster compared to the conventional oral dosing. A cartoon showing the pharmacokinetic profile in a typical patient for an intravenous loading dose followed by subsequent oral doses is shown in Figure 3.

Figure 3: Illustrative pharmacokinetic profile for an intravenous loading dose followed by subsequent oral doses in a typical patient.

16 HOW SUPPLIED/STORAGE AND HANDLING

Sotalol hydrochloride Injection is a clear and colorless solution as follows:

Each carton contains one single-dose vial containing 150 mg/10 mL (15 mg/mL) sotalol hydrochloride Injection

NDC 69724-112-10

Store at 20° to 25°C (68° to 77°F); excursions permitted 15° to 30°C (59° to 86°F) [See USP Controlled Room Temperature.] Protect from freezing and light.

17 PATIENT COUNSELING INFORMATION

17.1 Risk of hypoglycemia

Inform parents or caregivers that there is a risk of hypoglycemia when sotalol is given to patients who are fasting or who are vomiting. Inform patients to notify their healthcare provider if they experience symptoms of hypoglycemia. [ See Warnings and Precautions (5.7) ].

Manufactured by:
Mylan Institutional
Galway, Ireland

Manufactured for:
ALTATHERA Pharmaceuticals LLC
Chicago, IL 60606 U.S.A.

Principal Display Panel

NDC 69724-112-10

Sotalol Hydrochloride Injection

150 mg/ 10mL

(15mg/mL)

(13.3 mg/mL racemic sotalol)

For Intravenous Use Only

Rx Only

Single-Dose Vial